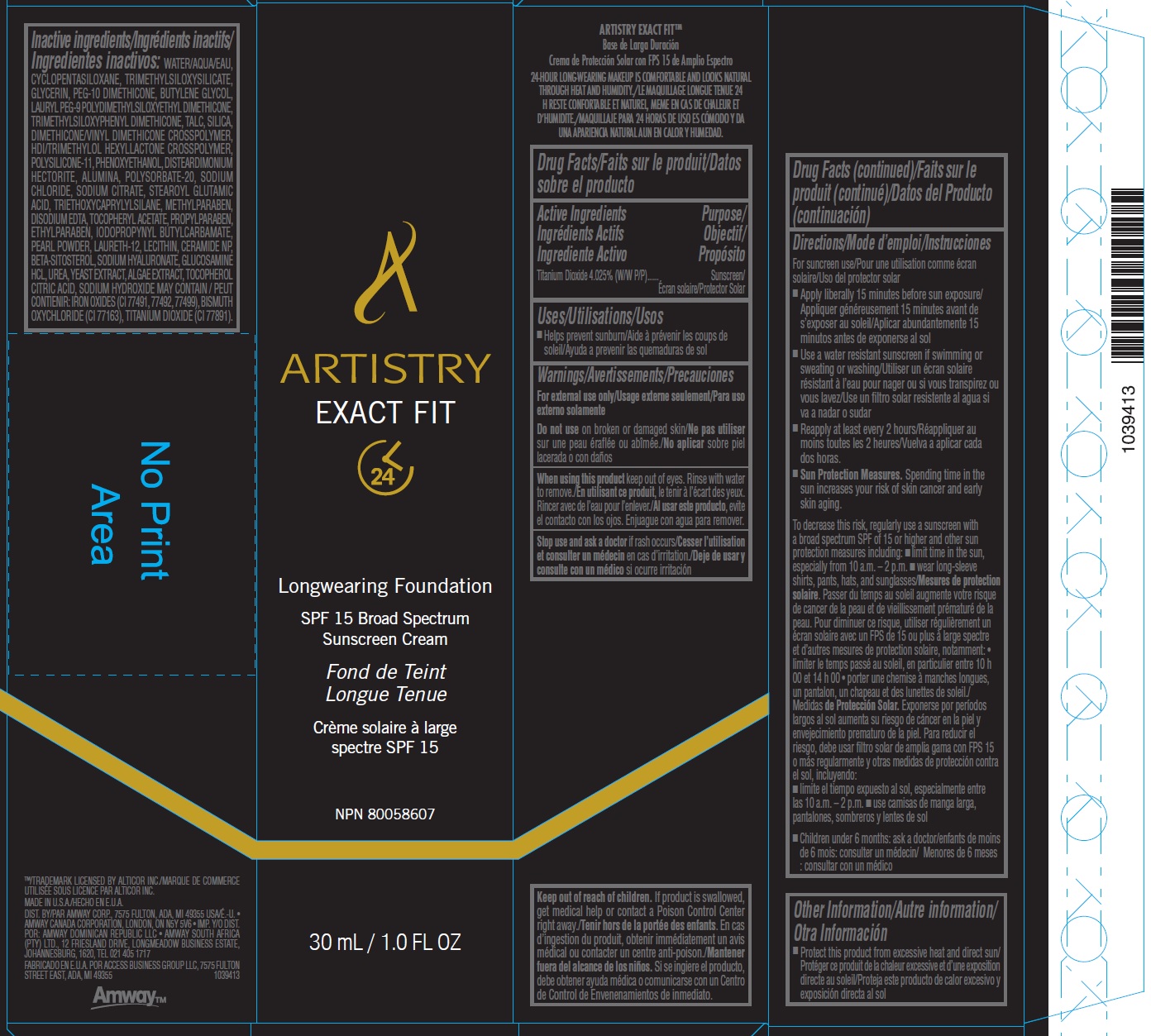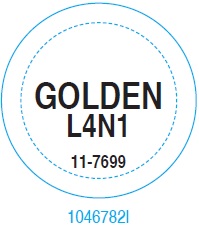 DRUG LABEL: 
                  Artistry Exact Fit Longwearing Foundation Shade Golden
                
                  

NDC: 50390-205 | Form: CREAM
Manufacturer: Amway Corp
Category: otc | Type: HUMAN OTC DRUG LABEL
Date: 20231022

ACTIVE INGREDIENTS: TITANIUM DIOXIDE 40.25 mg/1 mL
INACTIVE INGREDIENTS: EDETATE DISODIUM ANHYDROUS; .ALPHA.-TOCOPHEROL ACETATE; PROPYLPARABEN; ETHYLPARABEN; IODOPROPYNYL BUTYLCARBAMATE; PEARL (HYRIOPSIS CUMINGII); LAURETH-12; CERAMIDE NP; .BETA.-SITOSTEROL; HYALURONATE SODIUM; GLUCOSAMINE HYDROCHLORIDE; UREA; YEAST, UNSPECIFIED; TOCOPHEROL; CITRIC ACID MONOHYDRATE; SODIUM HYDROXIDE; WATER; CYCLOMETHICONE 5; GLYCERIN; PEG-10 DIMETHICONE (600 CST); BUTYLENE GLYCOL; LAURYL PEG-9 POLYDIMETHYLSILOXYETHYL DIMETHICONE; TALC; SILICON DIOXIDE; ALUMINUM OXIDE; POLYSORBATE 20; SODIUM CHLORIDE; SODIUM CITRATE; STEAROYL GLUTAMIC ACID; TRIETHOXYCAPRYLYLSILANE; METHYLPARABEN; HEXAMETHYLENE DIISOCYANATE/TRIMETHYLOL HEXYLLACTONE CROSSPOLYMER; DIMETHICONE/VINYL DIMETHICONE CROSSPOLYMER (SOFT PARTICLE); PHENOXYETHANOL; DISTEARDIMONIUM HECTORITE

Artistry Exact Fit™ Longwearing Foundation Shade Golden L4N1

Active Ingredients

Titanium Dioxide 4.025% (W/W P/P)

Purpose

Sunscreen

Uses

- Helps prevent sunburn

Warnings

For external use only

Do not use

on broken or damaged skin

When using this product

keep out of eyes. Rinse with water to remove.

Stop use and ask a doctor

if rash occurs

Keep out of reach of children.

If product is swallowed, get medical help or contact a Poison Control Center right away.

Directions

For suncreen use

- Apply liberally 15 minutes before sun exposure
- Use a water resistant sunscreen if swimming or sweating or washing
- Reapply at least every 2 hours
- Spending time in the sun increases your risk of skin cancer and early skin aging. Sun Protection Measures.
- To decrease this risk, regularly use a sunscreen with a broad spectrum SPF of 15 or higher and other sun protection measures including:
- limit time in the sun, especially from 10 a.m. – 2 p.m.
- wear long-sleeve shirts, pants, hats, and sunglasses
- Children under 6 months: ask a doctor

Other Information

- Protect this product from excessive heat and direct sun

Inactive ingredients

WATER/AQUA/EAU, CYCLOPENTASILOXANE, TRIMETHYLSILOXYSILICATE, GLYCERIN, PEG-10 DIMETHICONE, BUTYLENE GLYCOL, LAURYL PEG-9 POLYDIMETHYLSILOXYETHYL DIMETHICONE, TRIMETHYLSILOXYPHENYL DIMETHICONE, TALC, SILICA, DIMETHICONE/VINYL DIMETHICONE CROSSPOLYMER, HDI/TRIMETHYLOL HEXYLLACTONE CROSSPOLYMER, POLYSILICONE-11, PHENOXYETHANOL, DISTEARDIMONIUM HECTORITE, ALUMINA, POLYSORBATE-20, SODIUM CHLORIDE, SODIUM CITRATE, STEAROYL GLUTAMIC ACID, TRIETHOXYCAPRYLYLSILANE, METHYLPARABEN, DISODIUM EDTA, TOCOPHERYL ACETATE, PROPYLPARABEN, ETHYLPARABEN, IODOPROPYNYL BUTYLCARBAMATE, PEARL POWDER, LAURETH-12, LECITHIN, CERAMIDE NP, BETA-SITOSTEROL, SODIUM HYALURONATE, GLUCOSAMINE HCL, UREA, YEAST EXTRACT, ALGAE EXTRACT, TOCOPHEROL CITRIC ACID, SODIUM HYDROXIDE MAY CONTAIN / PEUT CONTIENIR: IRON OXIDES (CI 77491, 77492, 77499), BISMUTH OXYCHLORIDE (CI 77163), TITANIUM DIOXIDE (CI 77891).